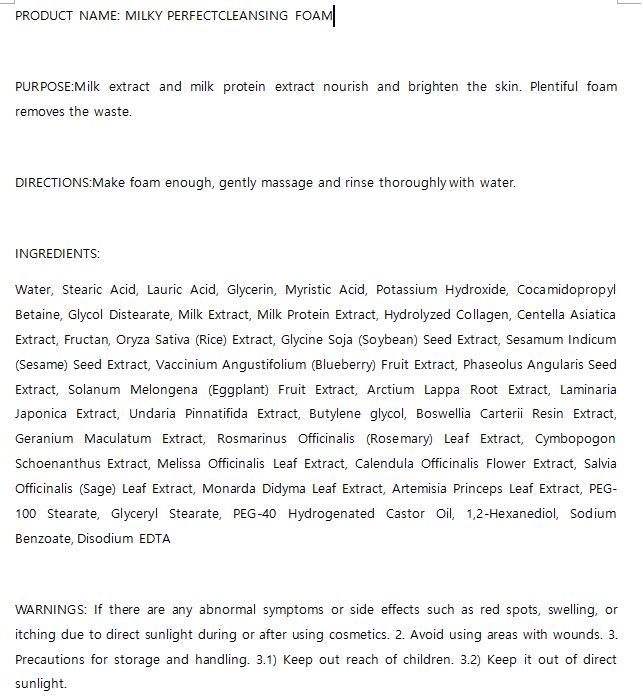 DRUG LABEL: W.SKIN MILKY PERFECT CLEANSING FOAM
NDC: 74997-0024 | Form: LIQUID
Manufacturer: J&J COMPANY
Category: otc | Type: HUMAN OTC DRUG LABEL
Date: 20210511

ACTIVE INGREDIENTS: CASEIN 0.1 g/100 mL
INACTIVE INGREDIENTS: WATER; GLYCERIN

ACTIVE INGREDIENT

Milk Protein Extract

INACTIVE INGREDIENT

Water, Stearic Acid, Lauric Acid, Glycerin, Myristic Acid, Potassium Hydroxide, Cocamidopropyl Betaine, Glycol Distearate, Milk Extract, Milk Protein Extract, Hydrolyzed Collagen, Centella Asiatica Extract, Fructan, Oryza Sativa (Rice) Extract, Glycine Soja (Soybean) Seed Extract, Sesamum Indicum (Sesame) Seed Extract, Vaccinium Angustifolium (Blueberry) Fruit Extract, Phaseolus Angularis Seed Extract, Solanum Melongena (Eggplant) Fruit Extract, Arctium Lappa Root Extract, Laminaria Japonica Extract, Undaria Pinnatifida Extract, Butylene glycol, Boswellia Carterii Resin Extract, Geranium Maculatum Extract, Rosmarinus Officinalis (Rosemary) Leaf Extract, Cymbopogon Schoenanthus Extract, Melissa Officinalis Leaf Extract, Calendula Officinalis Flower Extract, Salvia Officinalis (Sage) Leaf Extract, Monarda Didyma Leaf Extract, Artemisia Princeps Leaf Extract, PEG-100 Stearate, Glyceryl Stearate, PEG-40 Hydrogenated Castor Oil, 1,2-Hexanediol, Sodium Benzoate, Disodium EDTA

PURPOSE

Milk extract and milk protein extract nourish and brighten the skin. Plentiful foam removes the waste.

keep out of reach of the children

INDICATIONS AND USAGE

Make foam enough, gently massage and rinse thoroughly with water.

WARNINGS

If there are any abnormal symptoms or side effects such as red spots, swelling, or itching due to direct sunlight during or after using cosmetics. 2. Avoid using areas with wounds. 3. Precautions for storage and handling. 3.1) Keep out reach of children. 3.2) Keep it out of direct sunlight.

DOSAGE AND ADMINISTRATION

for external use only